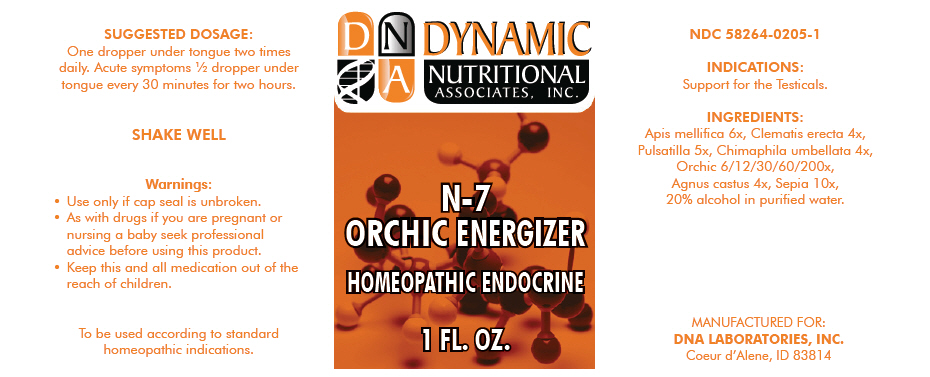 DRUG LABEL: N-7
NDC: 58264-0205 | Form: SOLUTION
Manufacturer: DNA Labs, Inc.
Category: homeopathic | Type: HUMAN OTC DRUG LABEL
Date: 20250109

ACTIVE INGREDIENTS: APIS MELLIFERA 6 [hp_X]/1 mL; CLEMATIS RECTA WHOLE 4 [hp_X]/1 mL; ANEMONE PULSATILLA 5 [hp_X]/1 mL; CHIMAPHILA UMBELLATA 4 [hp_X]/1 mL; SUS SCROFA TESTICLE 200 [hp_X]/1 mL; CHASTE TREE 4 [hp_X]/1 mL; SEPIA OFFICINALIS JUICE 10 [hp_X]/1 mL
INACTIVE INGREDIENTS: ALCOHOL; WATER

N-7

NDC 58264-0205-1

INDICATIONS

PURPOSE

Support for the Testicals.

INGREDIENTS

INACTIVE INGREDIENT

Apis mellifica 6x, Clematis erecta 4x, Pulsatilla 5x, Chimaphila umbellata 4x, Orchic 6/12/30/60/200x, Agnus castus 4x, Sepia 10x, 20% alcohol in purified water.

SUGGESTED DOSAGE

One dropper under tongue two times daily. Acute symptoms ½ dropper under tongue every 30 minutes for two hours.

STORAGE AND HANDLING

SHAKE WELL

Warnings

- Use only if cap seal is unbroken.

PREGNANCY OR BREAST FEEDING

- As with drugs if you are pregnant or nursing a baby seek professional advice before using this product.

KEEP OUT OF REACH OF CHILDREN

- Keep this and all medication out of the reach of children.

To be used according to standard homeopathic indications.

PRINCIPAL DISPLAY PANEL - 1 FL. OZ. Bottle Label

DYNAMIC
NUTRITIONAL
ASSOCIATES, INC.

N-7
ORCHIC ENERGIZER

HOMEOPATHIC ENDOCRINE

1 FL. OZ.